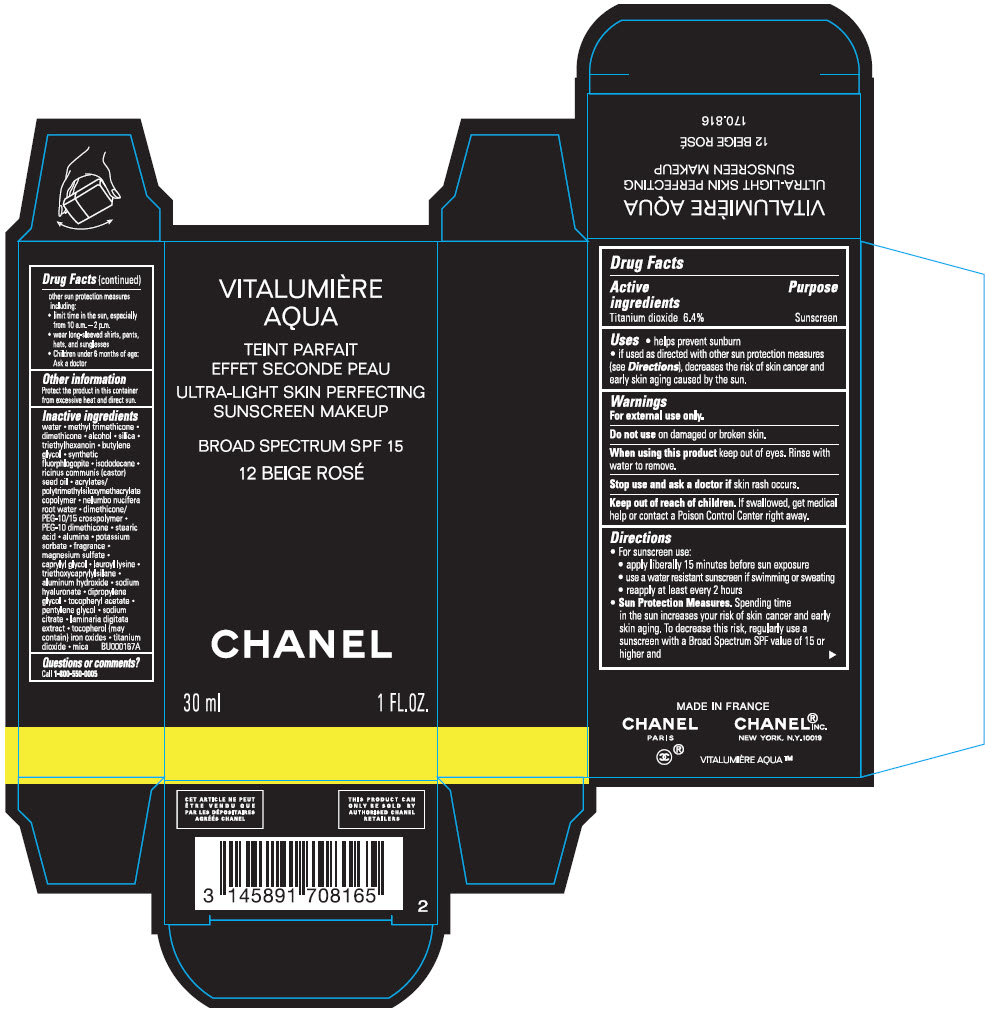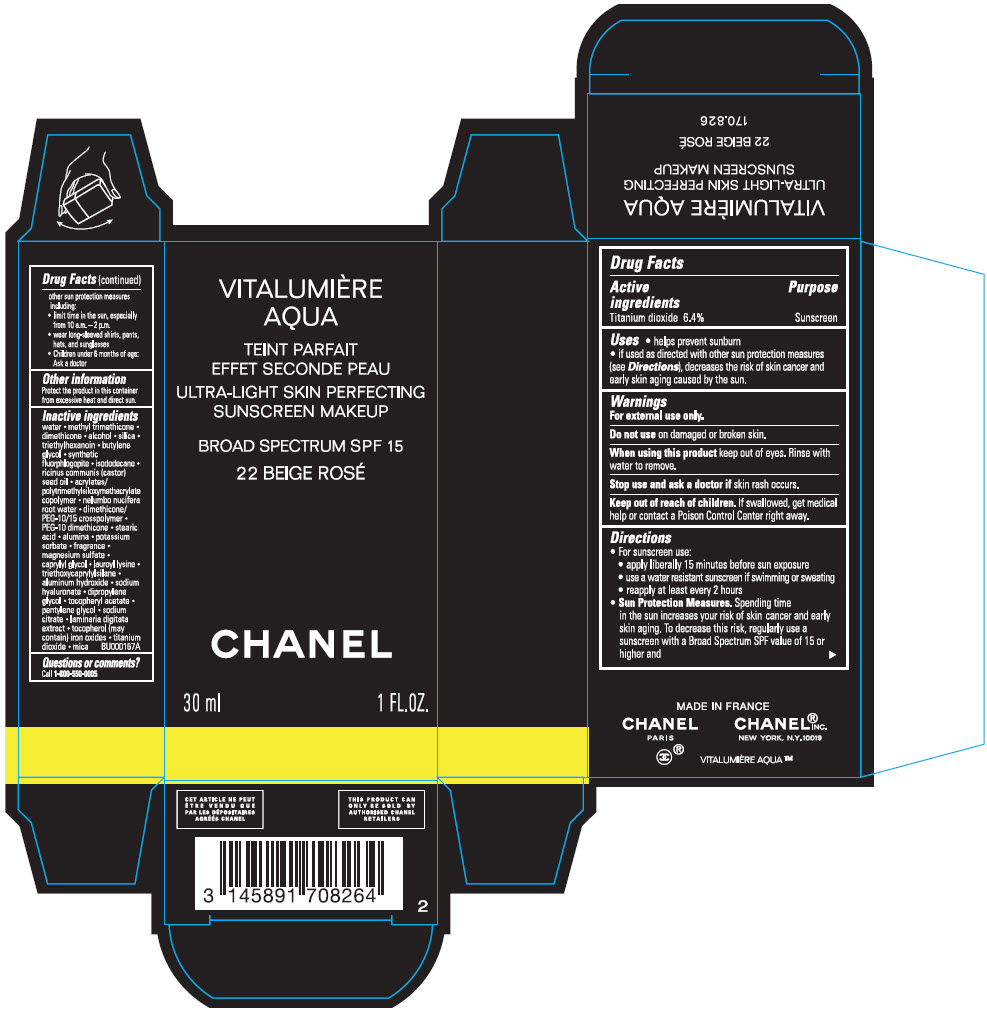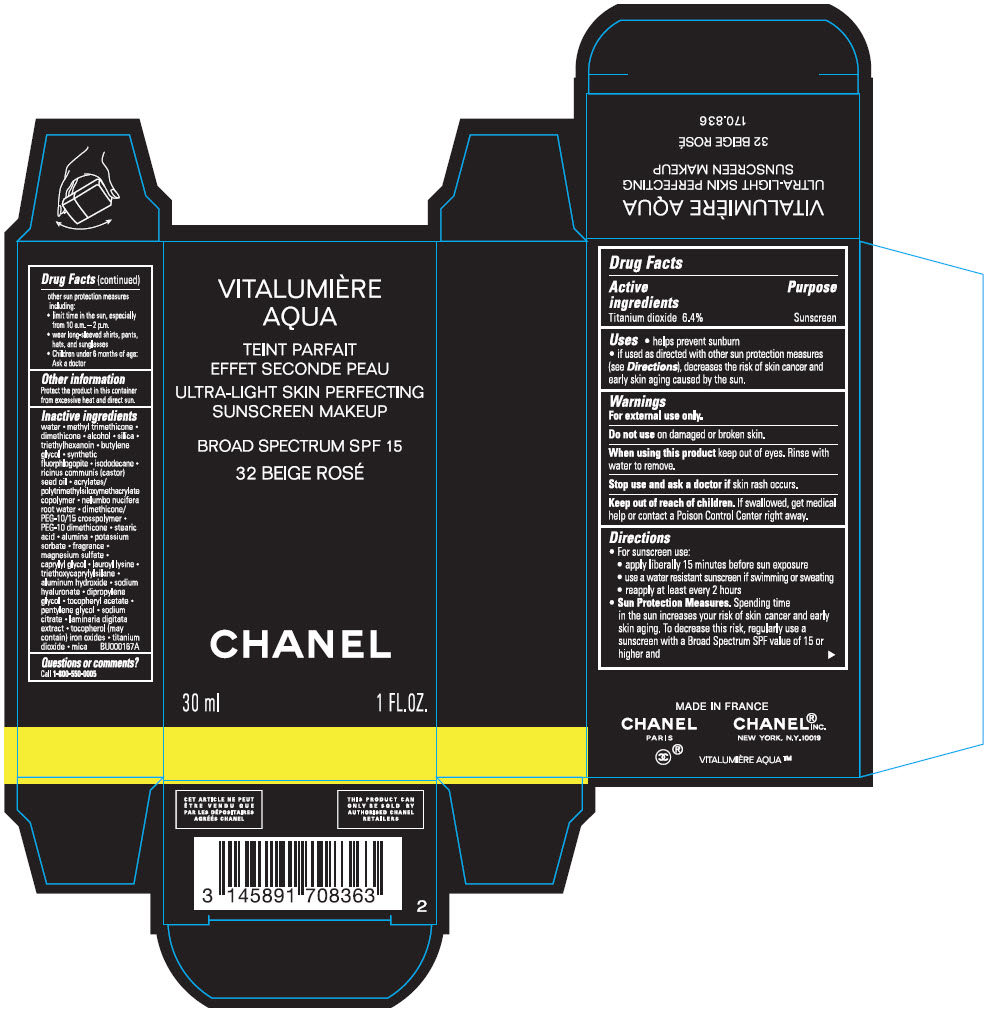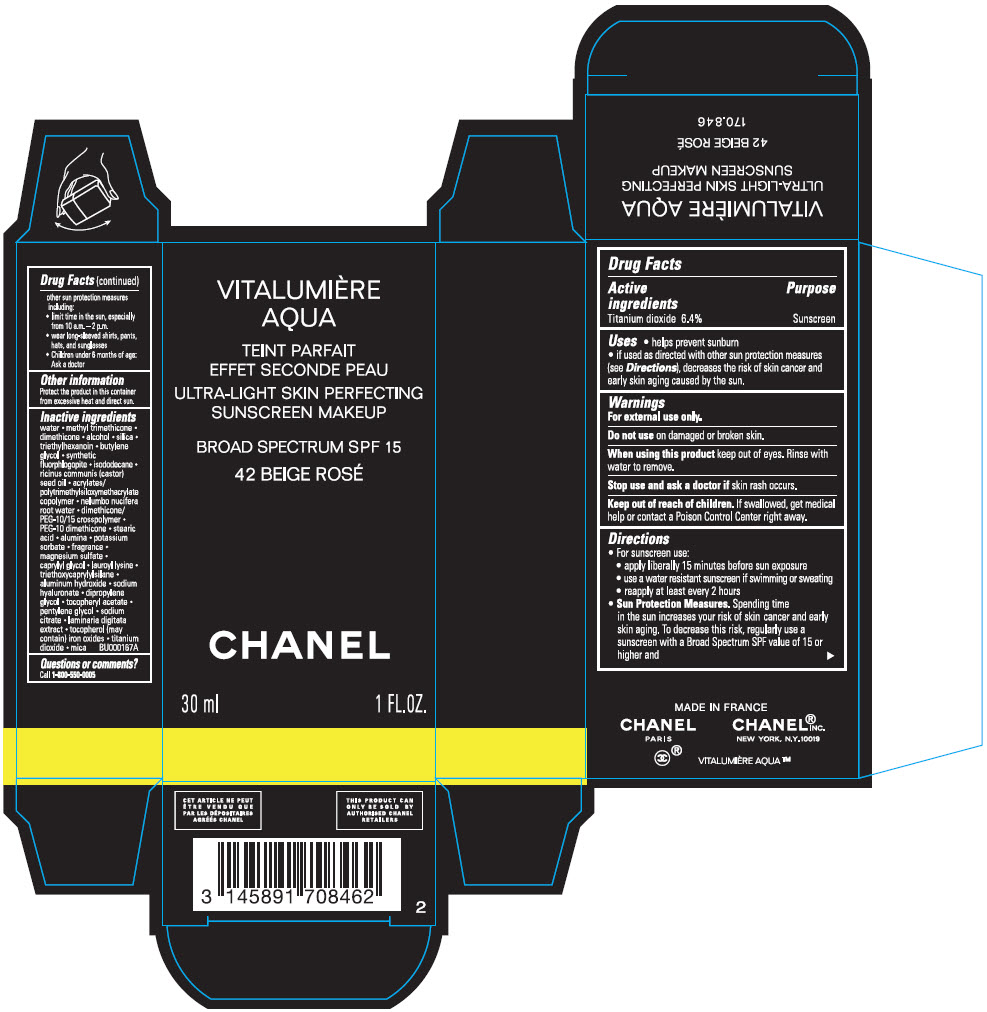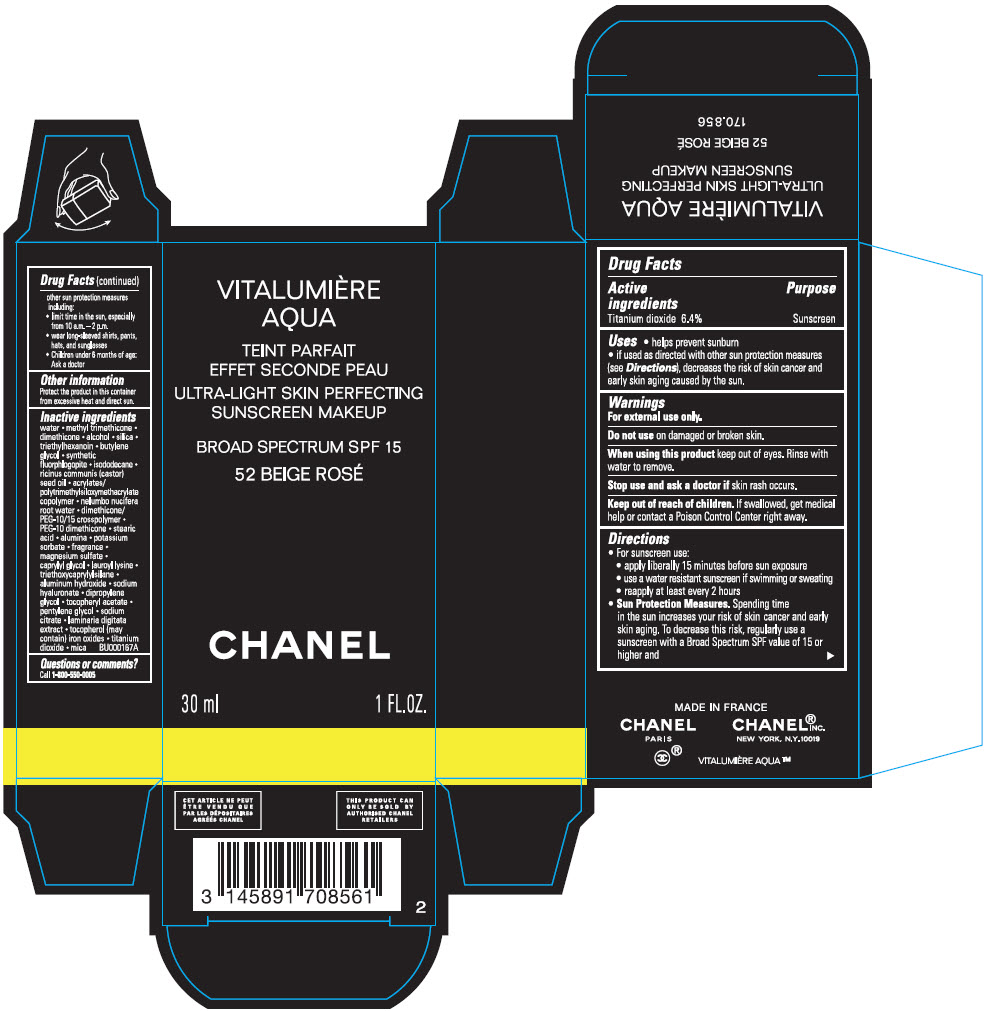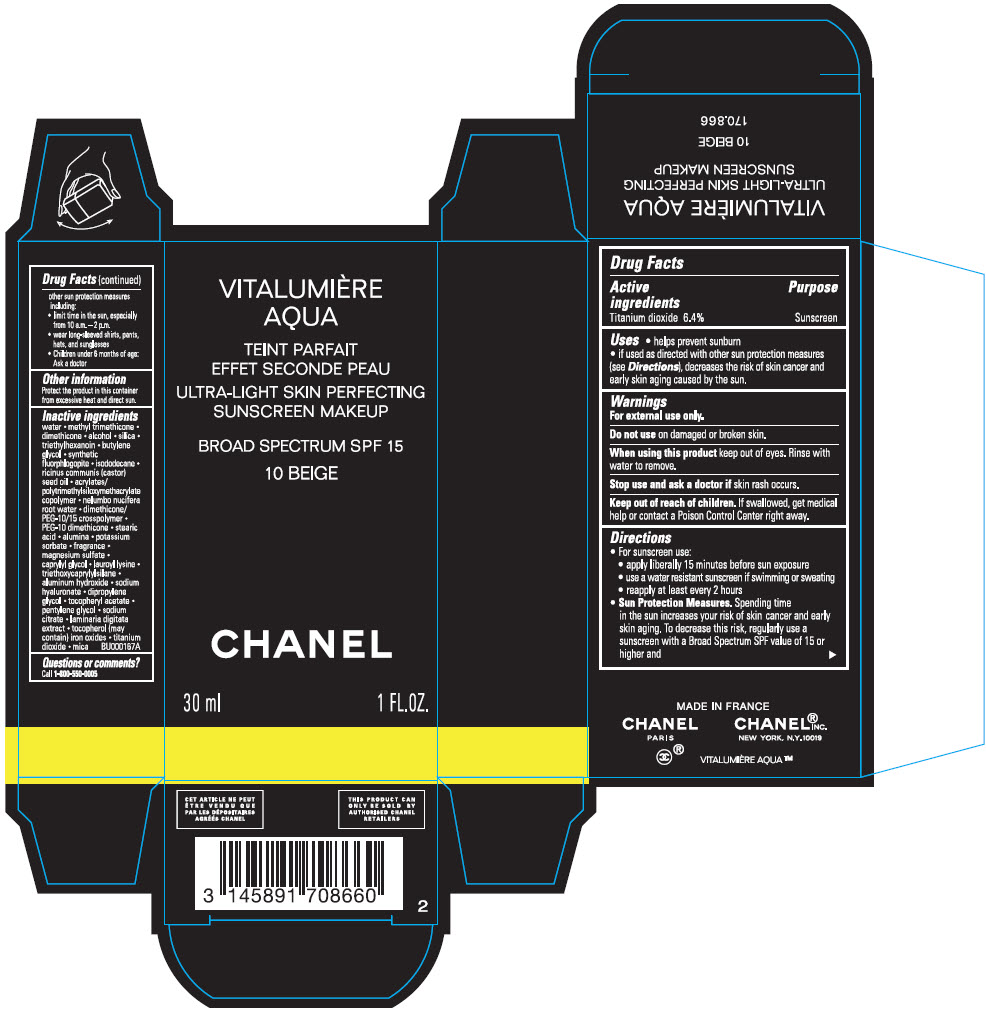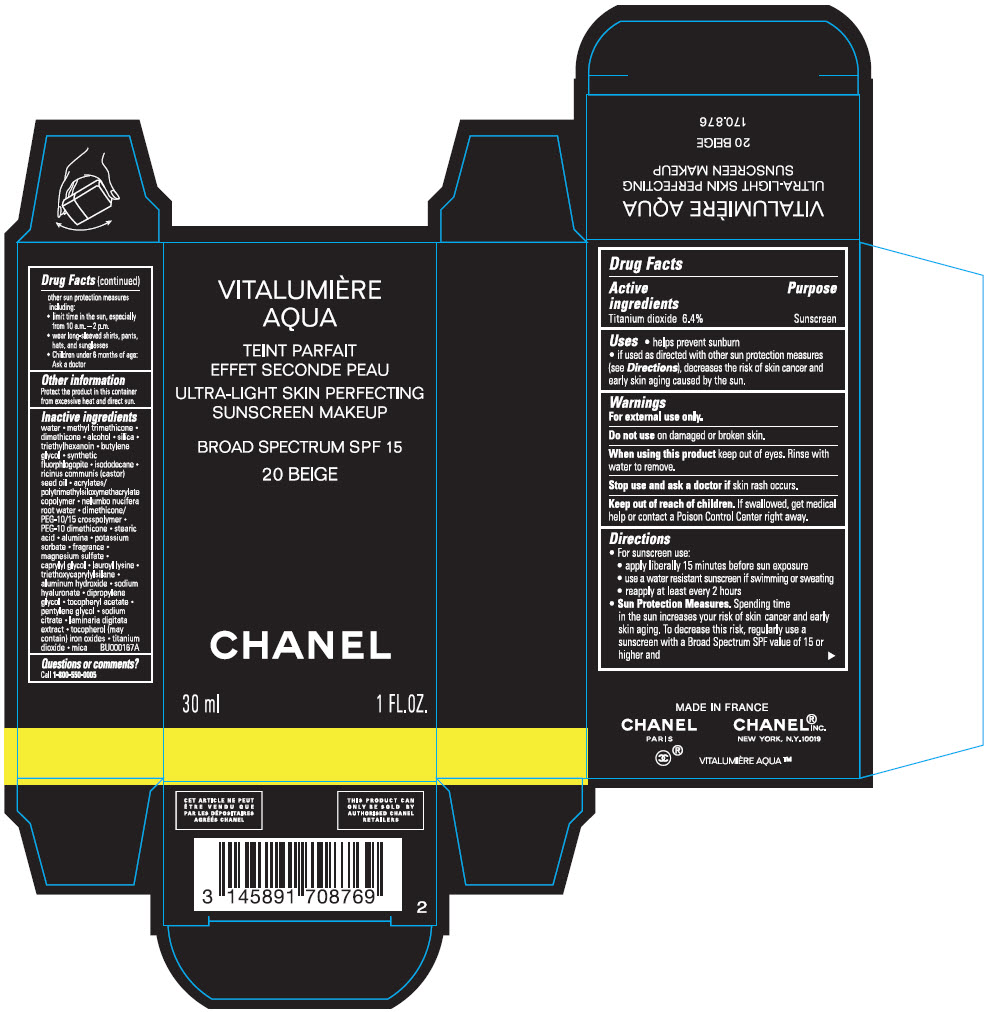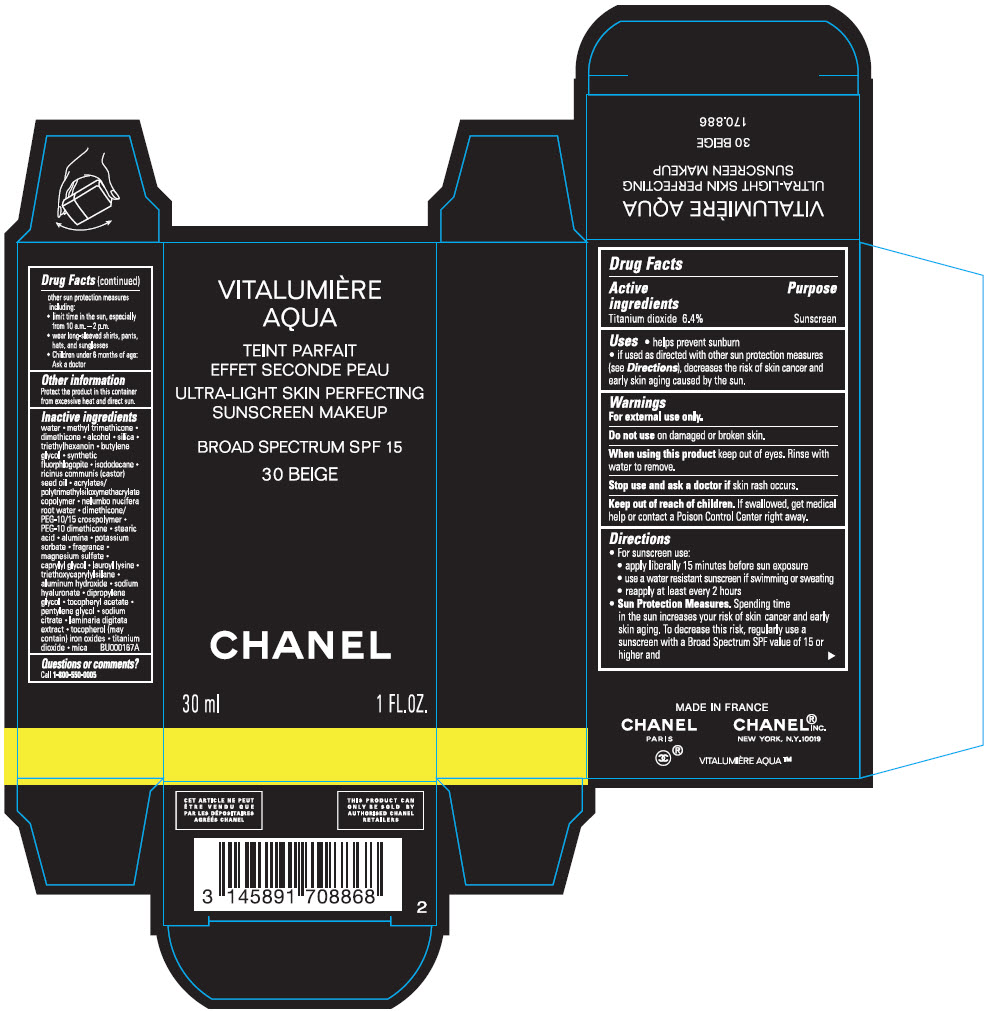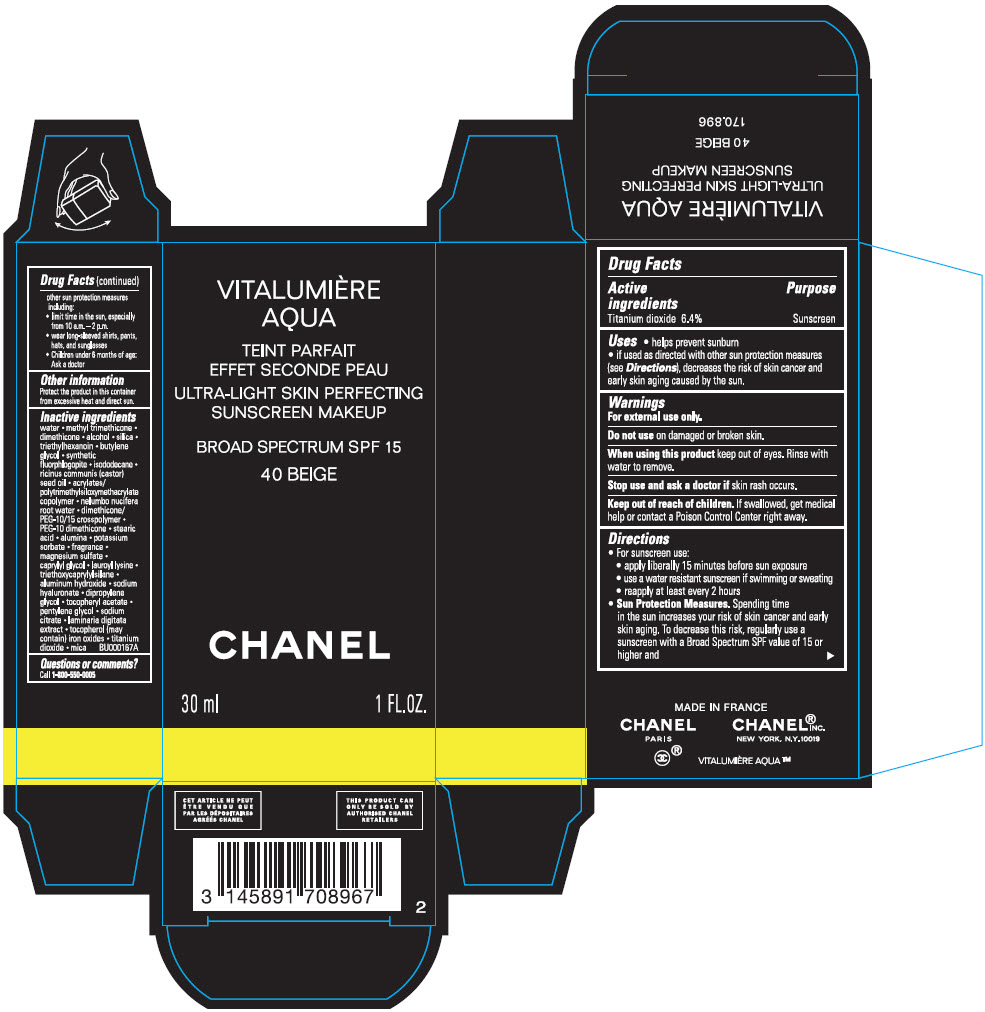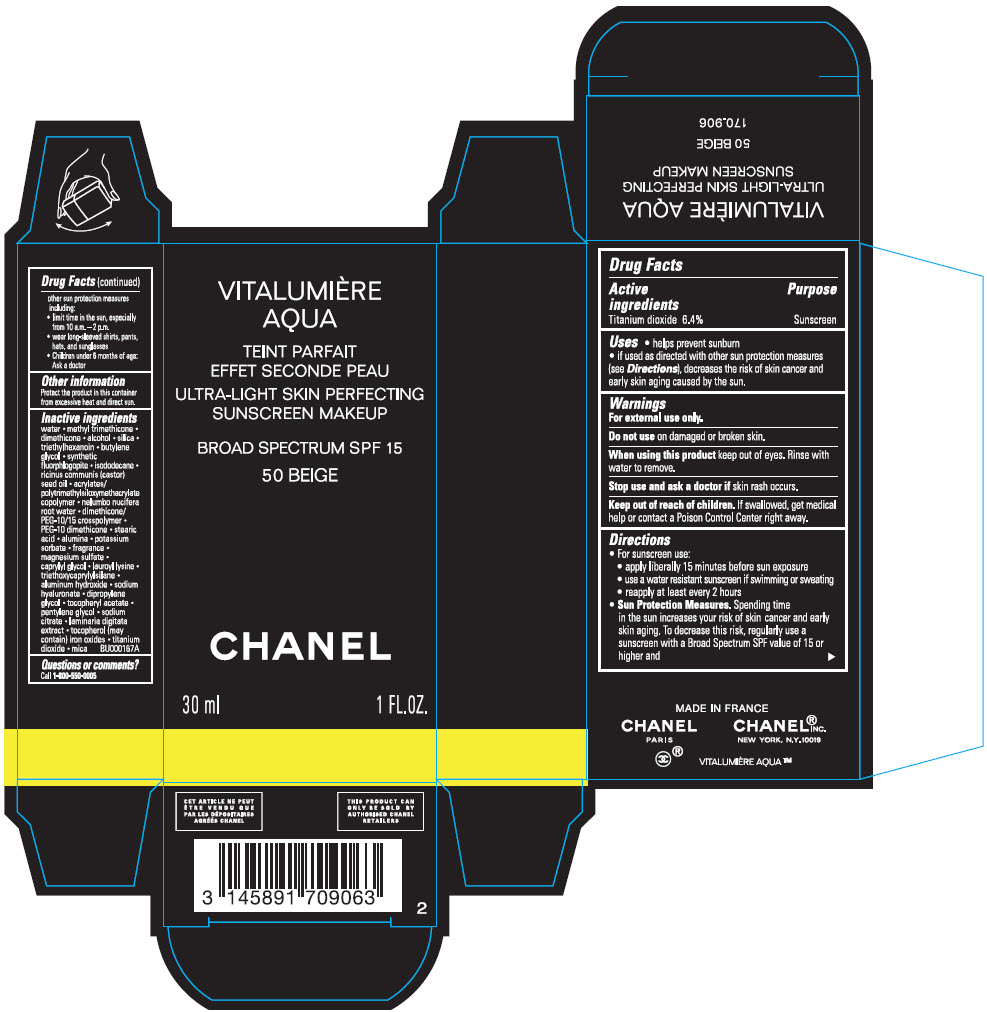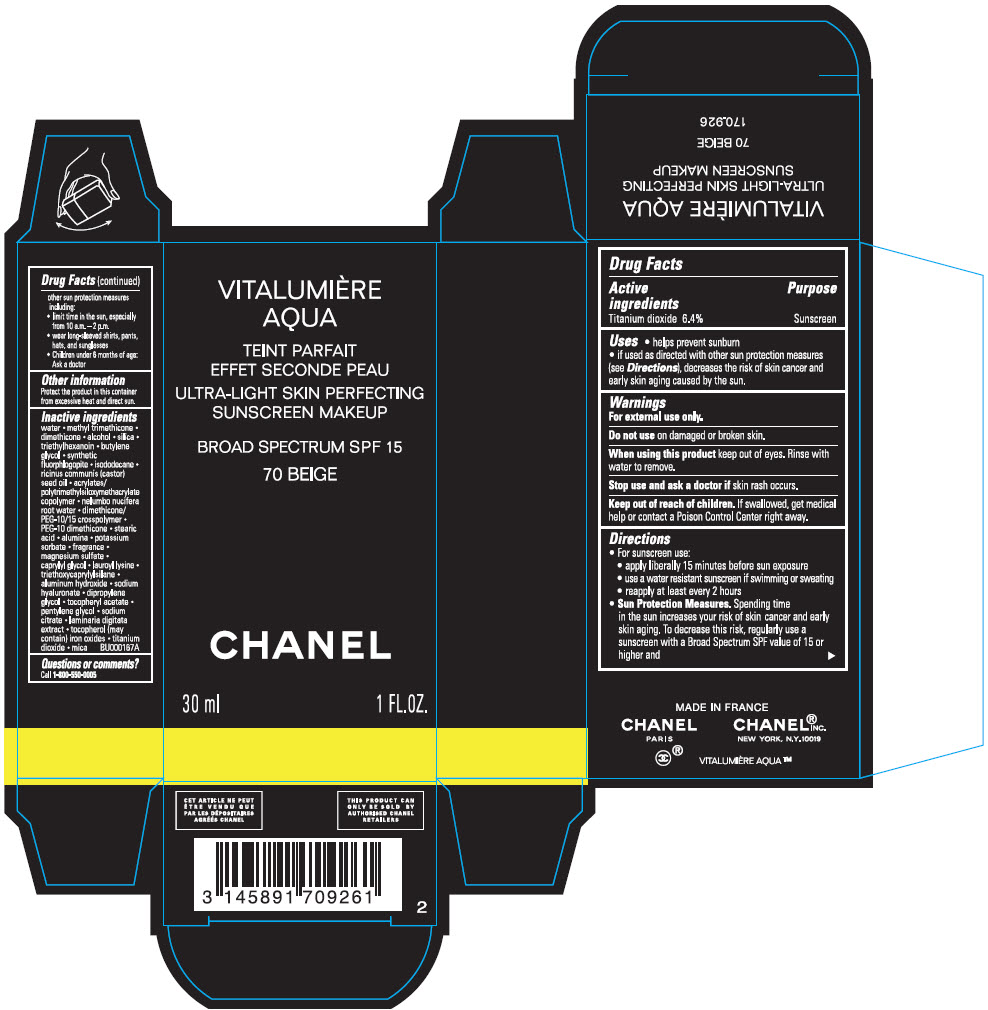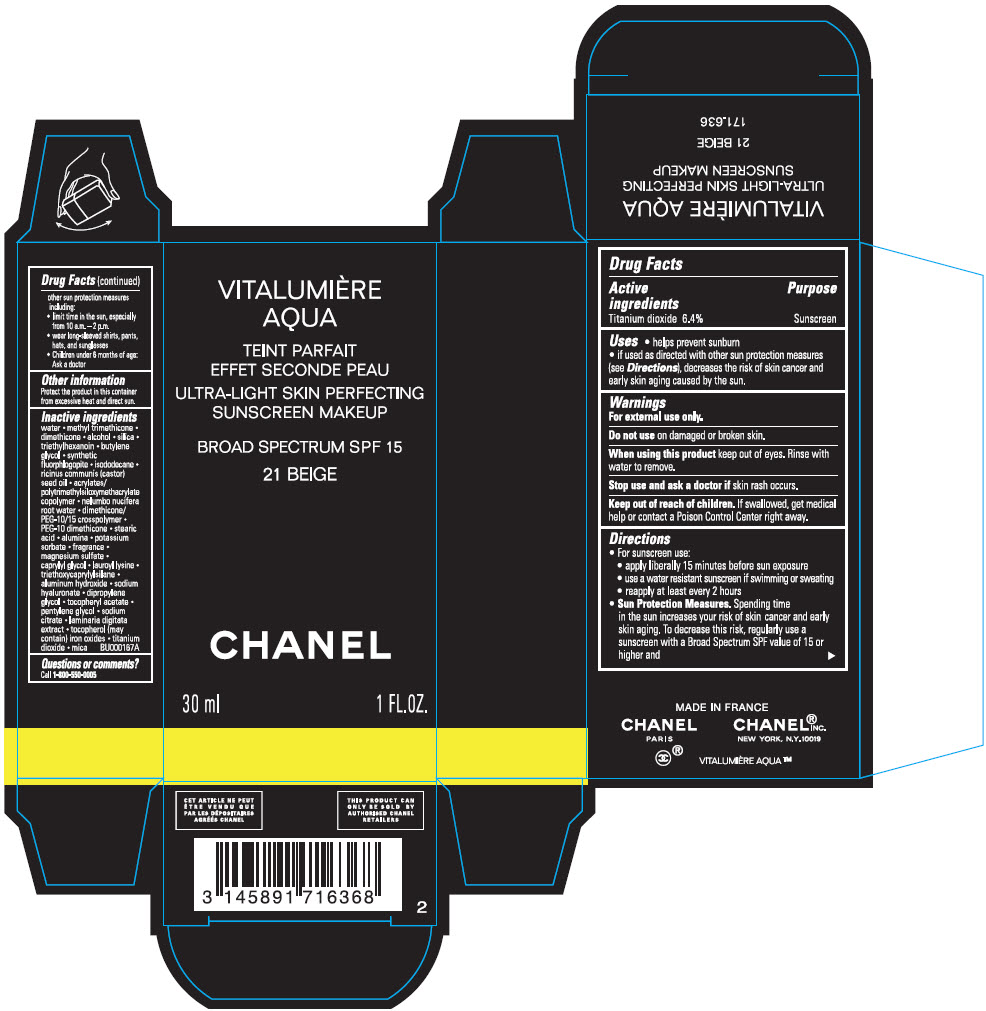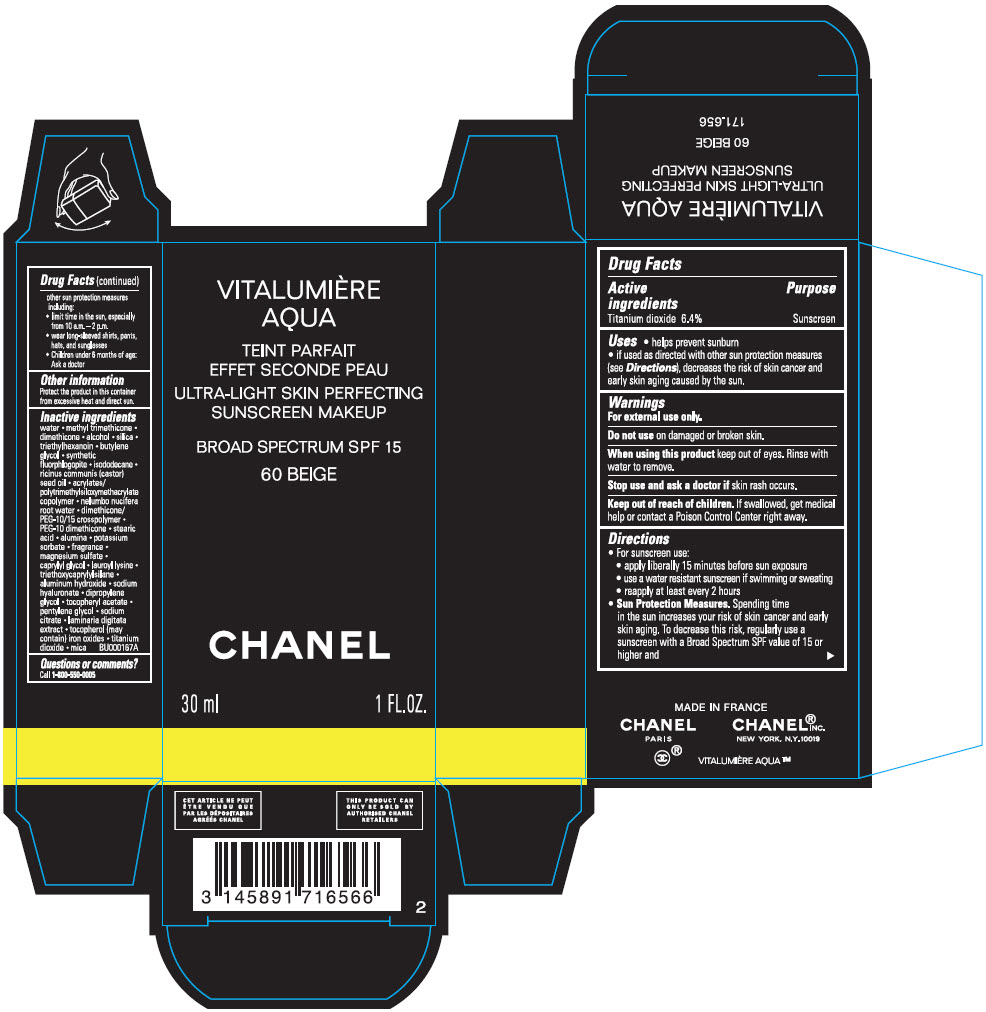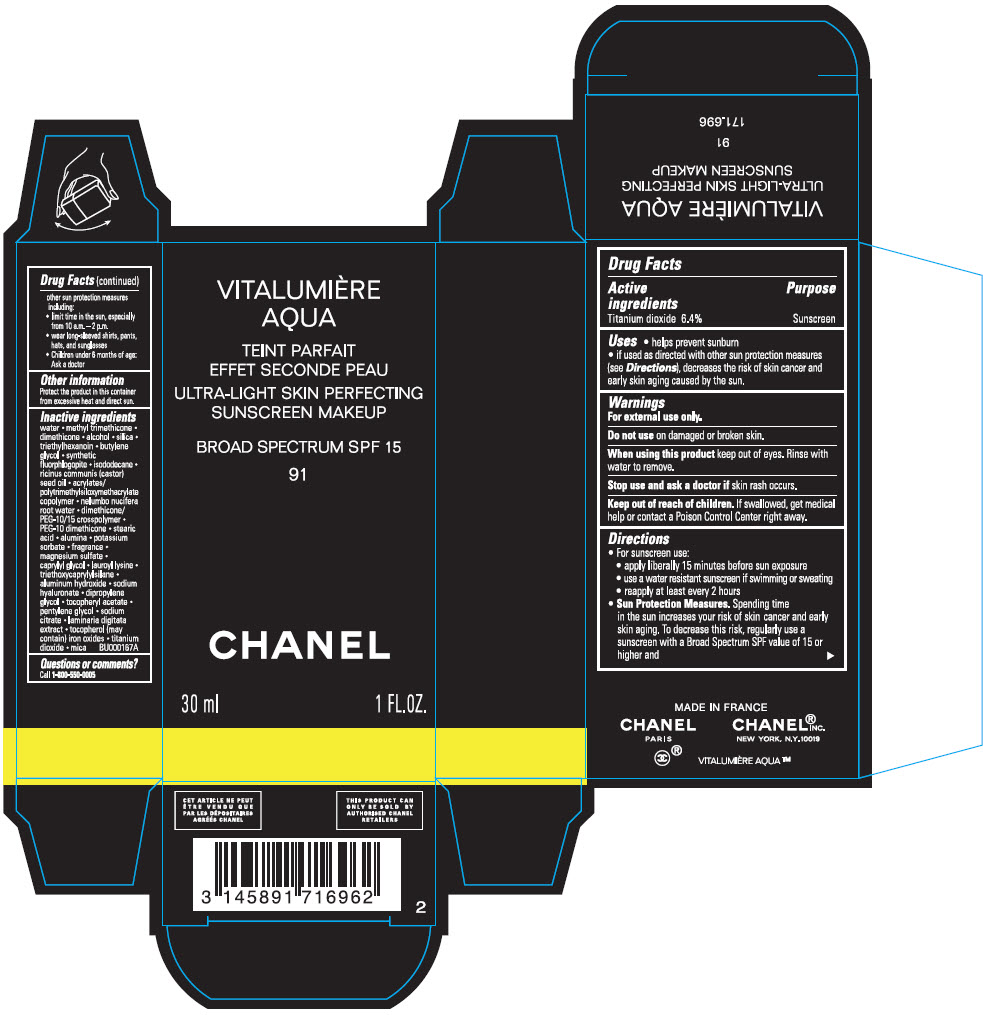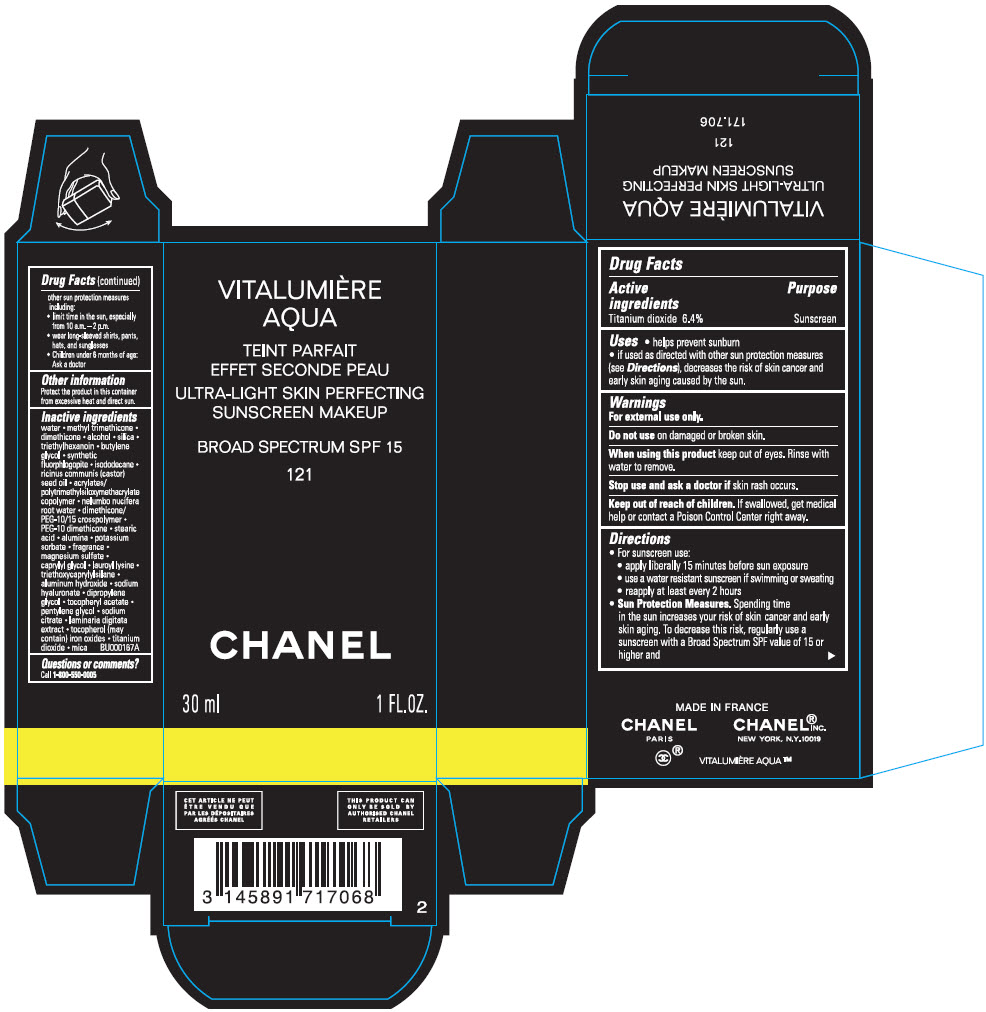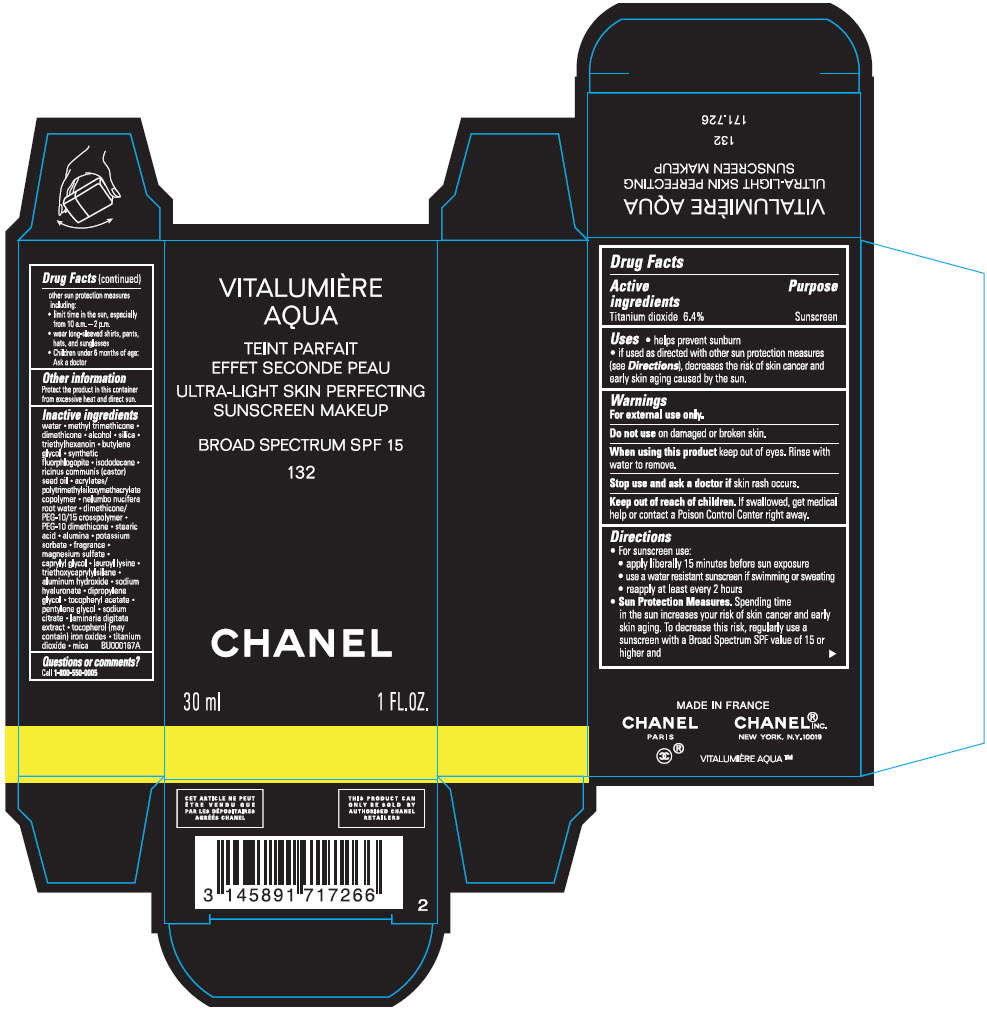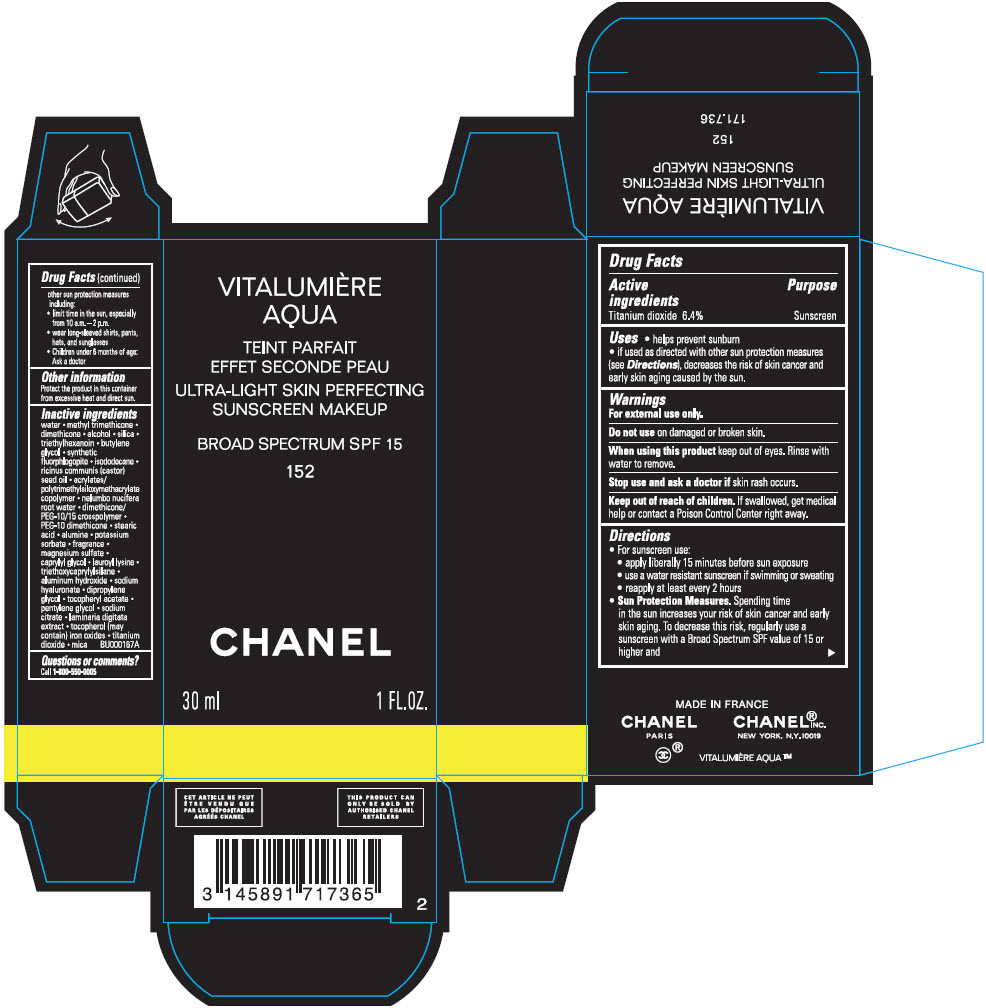 DRUG LABEL: VITALUMIERE AQUA 
NDC: 68745-2133 | Form: EMULSION
Manufacturer: CHANEL PARFUMS BEAUTE
Category: otc | Type: HUMAN OTC DRUG LABEL
Date: 20251111

ACTIVE INGREDIENTS: TITANIUM DIOXIDE 64 mg/1 mL
INACTIVE INGREDIENTS: WATER; METHYL TRIMETHICONE; DIMETHICONE; ALCOHOL; SILICON DIOXIDE; TRIETHYLHEXANOIN; BUTYLENE GLYCOL; MAGNESIUM POTASSIUM ALUMINOSILICATE FLUORIDE; ISODODECANE; CASTOR OIL; DIMETHICONE/PEG-10/15 CROSSPOLYMER; NELUMBO NUCIFERA ROOT OIL; PEG-10 DIMETHICONE (600 CST); STEARIC ACID; ALUMINUM OXIDE; POTASSIUM SORBATE; MAGNESIUM SULFATE, UNSPECIFIED FORM; CAPRYLYL GLYCOL; LAUROYL LYSINE; TRIETHOXYCAPRYLYLSILANE; HYALURONATE SODIUM; ALUMINUM HYDROXIDE; DIPROPYLENE GLYCOL; .ALPHA.-TOCOPHEROL ACETATE; PENTYLENE GLYCOL; SODIUM CITRATE, UNSPECIFIED FORM; LAMINARIA DIGITATA; TOCOPHEROL; FERRIC OXIDE YELLOW; FERRIC OXIDE RED; FERROSOFERRIC OXIDE; MICA

VITALUMIERE AQUA
ULTRA-LIGHT SKIN PERFECTING SUNSCREEN MAKEUP BROAD SPECTRUM SPF 15

Drug Facts

Active ingredient

Titanium dioxide 6.4%

Purpose

Sunscreen

Uses

- helps prevent sunburn
- if used as directed with other sun protection measures (see Directions), decreases the risk of skin cancer and early skin aging caused by the sun.

Warnings

For external use only.

Do not use on damaged or broken skin.

When using this product keep out of eyes. Rinse with water to remove.

Stop use and ask a doctor if skin rash occurs.

Keep out of reach of children.

If swallowed, get medical help or contact a Poison Control Center right away.

Directions

- For sunscreen use:
  - apply liberally 15 minutes before sun exposure
  - use a water resistant sunscreen if swimming or sweating
  - reapply at least every 2 hours
- Sun Protection Measures. Spending time in the sun increases your risk of skin cancer and early skin aging. To decrease this risk, regularly use a sunscreen with a Broad Spectrum SPF value of 15 or higher and other sun protection measures including:
  - limit time in the sun, especially from 10 a.m. – 2 p.m.
  - wear long-sleeved shirts, pants, hats, and sunglasses
  - Children under 6 months of age: Ask a doctor

Other information

Protect the product in this container from excessive heat and direct sun.

Inactive ingredients

water ∙ methyl trimethicone ∙ dimethicone ∙ alcohol ∙ silica ∙ triethylhexanoin ∙ butylene glycol ∙ synthetic fluorphlogopite ∙ isododecane ∙ ricinus communis (castor) seed oil ∙ acrylates/polytrimethylsiloxymethacrylate copolymer ∙ nelumbo nucifera root water ∙ dimethicone/PEG-10/15 crosspolymer ∙ PEG-10 dimethicone ∙ stearic acid ∙ alumina ∙ potassium sorbate ∙ fragrance ∙ magnesium sulfate ∙ caprylyl glycol ∙ lauroyl lysine ∙ triethoxycaprylylsilane ∙ sodium hyaluronate ∙ dipropylene glycol ∙ tocopheryl acetate ∙ pentylene glycol ∙ sodium citrate ∙ laminaria digitata extract ∙ tocopherol (may contain) iron oxides ∙ titanium dioxide ∙ mica
BU000167A

Questions or comments?

Call 1-800-550-0005

PRINCIPAL DISPLAY PANEL - 30 ml Bottle Carton - 12 BEIGE ROSÉ

VITALUMIÈRE
AQUA

ULTRA-LIGHT SKIN PERFECTING
SUNSCREEN MAKEUP

BROAD SPECTRUM SPF 15

12 BEIGE ROSÉ

CHANEL

30 ml
1 FL.OZ.

PRINCIPAL DISPLAY PANEL - 30 ml Bottle Carton - 22 BEIGE ROSÉ

VITALUMIÈRE
AQUA

ULTRA-LIGHT SKIN PERFECTING
SUNSCREEN MAKEUP

BROAD SPECTRUM SPF 15

22 BEIGE ROSÉ

CHANEL

30 ml
1 FL.OZ.

PRINCIPAL DISPLAY PANEL - 30 ml Bottle Carton - 32 BEIGE ROSÉ

VITALUMIÈRE
AQUA

ULTRA-LIGHT SKIN PERFECTING
SUNSCREEN MAKEUP

BROAD SPECTRUM SPF 15

32 BEIGE ROSÉ

CHANEL

30 ml
1 FL.OZ.

PRINCIPAL DISPLAY PANEL - 30 ml Bottle Carton - 42 BEIGE ROSÉ

VITALUMIÈRE
AQUA

ULTRA-LIGHT SKIN PERFECTING
SUNSCREEN MAKEUP

BROAD SPECTRUM SPF 15

42 BEIGE ROSÉ

CHANEL

30 ml
1 FL.OZ.

PRINCIPAL DISPLAY PANEL - 30 ml Bottle Carton - 52 BEIGE ROSÉ

VITALUMIÈRE
AQUA

ULTRA-LIGHT SKIN PERFECTING
SUNSCREEN MAKEUP

BROAD SPECTRUM SPF 15

52 BEIGE ROSÉ

CHANEL

30 ml
1 FL.OZ.

PRINCIPAL DISPLAY PANEL - 30 ml Bottle Carton - 10 BEIGE

VITALUMIÈRE
AQUA

ULTRA-LIGHT SKIN PERFECTING
SUNSCREEN MAKEUP

BROAD SPECTRUM SPF 15

10 BEIGE

CHANEL

30 ml
1 FL.OZ.

PRINCIPAL DISPLAY PANEL - 30 ml Bottle Carton - 20 BEIGE

VITALUMIÈRE
AQUA

ULTRA-LIGHT SKIN PERFECTING
SUNSCREEN MAKEUP

BROAD SPECTRUM SPF 15

20 BEIGE

CHANEL

30 ml
1 FL.OZ.

PRINCIPAL DISPLAY PANEL - 30 ml Bottle Carton - 30 BEIGE

VITALUMIÈRE
AQUA

ULTRA-LIGHT SKIN PERFECTING
SUNSCREEN MAKEUP

BROAD SPECTRUM SPF 15

30 BEIGE

CHANEL

30 ml
1 FL.OZ.

PRINCIPAL DISPLAY PANEL - 30 ml Bottle Carton - 40 BEIGE

VITALUMIÈRE
AQUA

ULTRA-LIGHT SKIN PERFECTING
SUNSCREEN MAKEUP

BROAD SPECTRUM SPF 15

40 BEIGE

CHANEL

30 ml
1 FL.OZ.

PRINCIPAL DISPLAY PANEL - 30 ml Bottle Carton - 50 BEIGE

VITALUMIÈRE
AQUA

ULTRA-LIGHT SKIN PERFECTING
SUNSCREEN MAKEUP

BROAD SPECTRUM SPF 15

50 BEIGE

CHANEL

30 ml
1 FL.OZ.

PRINCIPAL DISPLAY PANEL - 30 ml Bottle Carton - 70 BEIGE

VITALUMIÈRE
AQUA

ULTRA-LIGHT SKIN PERFECTING
SUNSCREEN MAKEUP

BROAD SPECTRUM SPF 15

70 BEIGE

CHANEL

30 ml
1 FL.OZ.

PRINCIPAL DISPLAY PANEL - 30 ml Bottle Carton - 21 BEIGE

VITALUMIÈRE
AQUA

ULTRA-LIGHT SKIN PERFECTING
SUNSCREEN MAKEUP

BROAD SPECTRUM SPF 15

21 BEIGE

CHANEL

30 ml
1 FL.OZ.

PRINCIPAL DISPLAY PANEL - 30 ml Bottle Carton - 60 BEIGE

VITALUMIÈRE
AQUA

ULTRA-LIGHT SKIN PERFECTING
SUNSCREEN MAKEUP

BROAD SPECTRUM SPF 15

60 BEIGE

CHANEL

30 ml
1 FL.OZ.

PRINCIPAL DISPLAY PANEL - 30 ml Bottle Carton - 91

VITALUMIÈRE
AQUA

ULTRA-LIGHT SKIN PERFECTING
SUNSCREEN MAKEUP

BROAD SPECTRUM SPF 15

91

CHANEL

30 ml
1 FL.OZ.

PRINCIPAL DISPLAY PANEL - 30 ml Bottle Carton - 121

VITALUMIÈRE
AQUA

ULTRA-LIGHT SKIN PERFECTING
SUNSCREEN MAKEUP

BROAD SPECTRUM SPF 15

121

CHANEL

30 ml
1 FL.OZ.

PRINCIPAL DISPLAY PANEL - 30 ml Bottle Carton - 132

VITALUMIÈRE
AQUA

ULTRA-LIGHT SKIN PERFECTING
SUNSCREEN MAKEUP

BROAD SPECTRUM SPF 15

132

CHANEL

30 ml
1 FL.OZ.

PRINCIPAL DISPLAY PANEL - 30 ml Bottle Carton - 152

VITALUMIÈRE
AQUA

ULTRA-LIGHT SKIN PERFECTING
SUNSCREEN MAKEUP

BROAD SPECTRUM SPF 15

152

CHANEL

30 ml
1 FL.OZ.